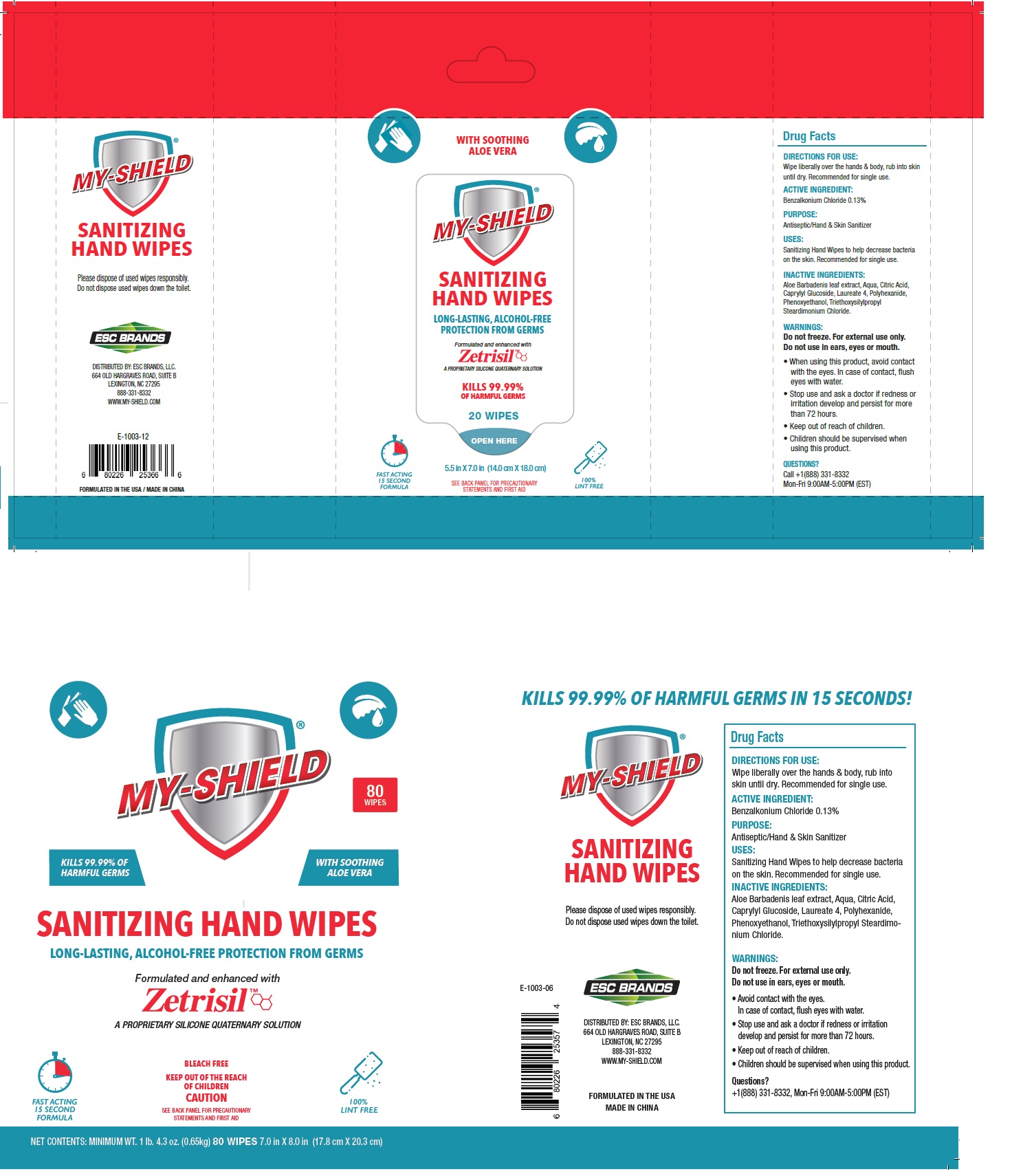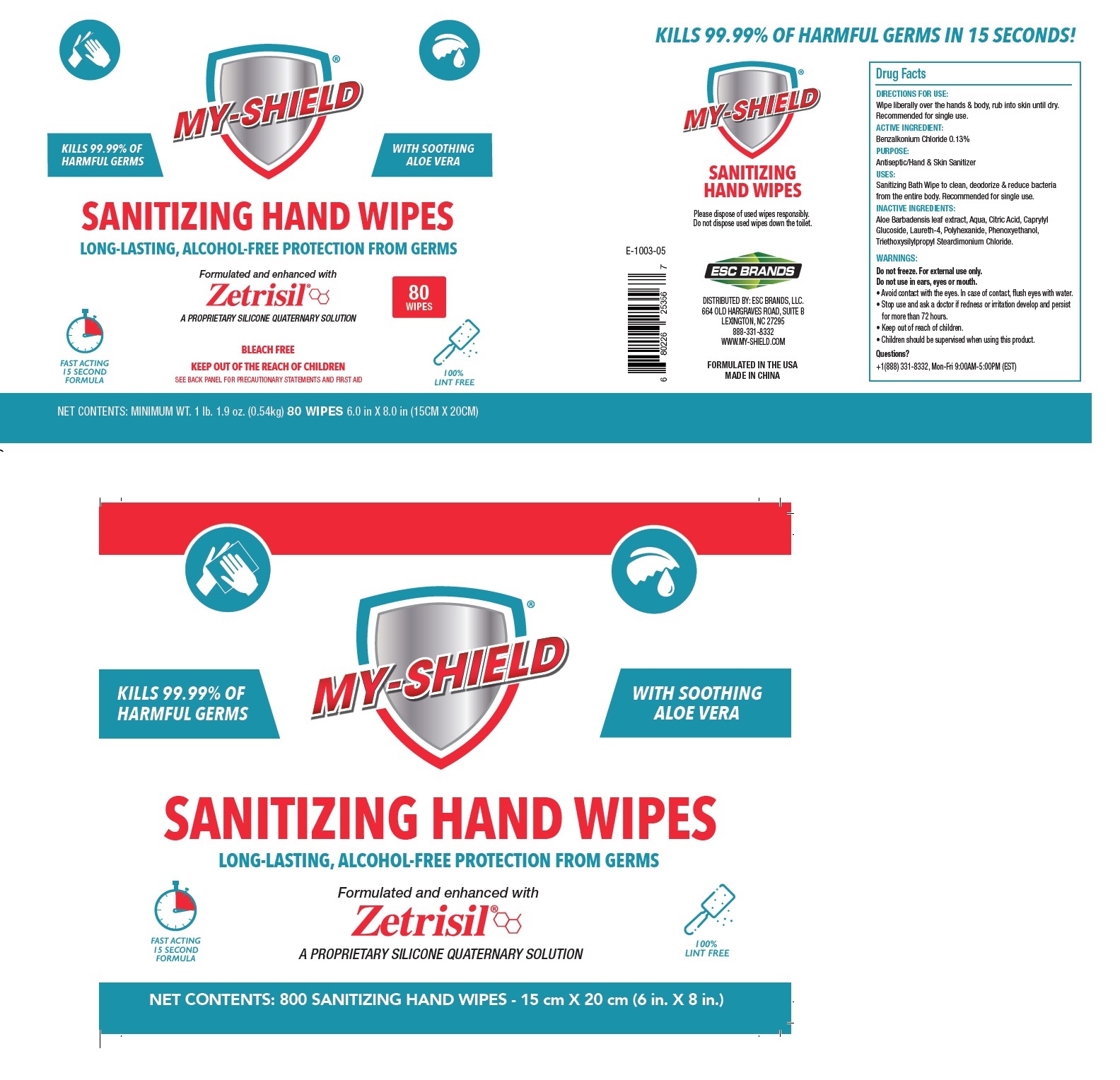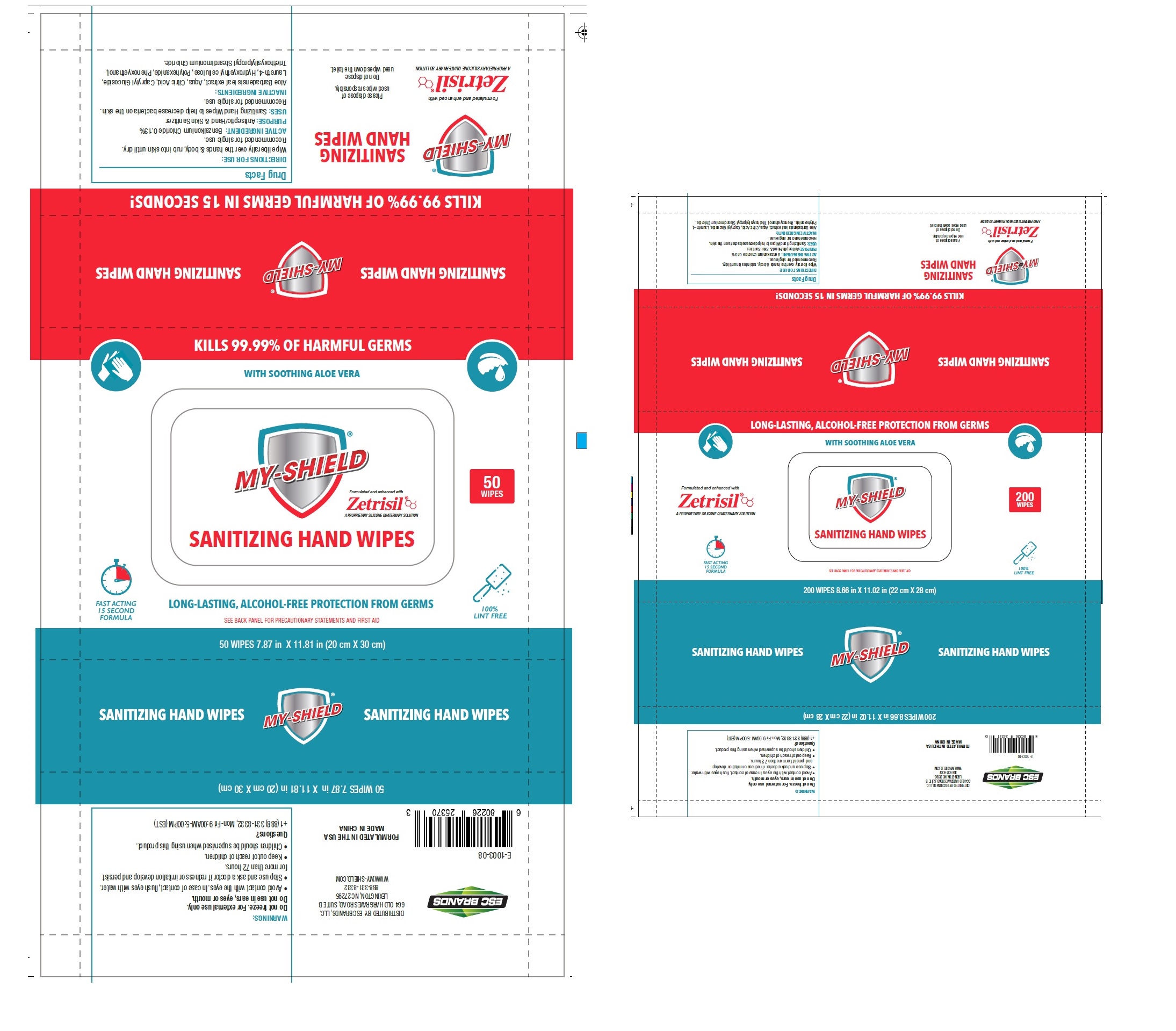 DRUG LABEL: My-Shield Sanitizing Hand Wipes
NDC: 71884-010 | Form: SWAB
Manufacturer: ENVIRO SPECIALTY CHEMICALS INC
Category: otc | Type: HUMAN OTC DRUG LABEL
Date: 20250120

ACTIVE INGREDIENTS: BENZALKONIUM CHLORIDE 1.3 mg/1 g
INACTIVE INGREDIENTS: ALOE VERA LEAF; WATER; CITRIC ACID MONOHYDRATE; CAPRYLYL GLUCOSIDE; LAURETH-4; POLIHEXANIDE; PHENOXYETHANOL; TRIETHOXYSILYLPROPYL STEARDIMONIUM CHLORIDE

MY-SHIELD SANITIZING HAND WIPES

ACTIVE INGREDIENT:

Benzalkonium Chloride 0.13%

PURPOSE:

Antiseptic/Hand & Skin Sanitizer

USES:

Sanitizing Hand Wipes to help decrease bacteria on the skin. Recommended for single use.

WARNINGS:

Do not freeze. For external use only.

Do not use in ears, eyes or mouth.

• When using this product, avoid contact with the eyes. In case of contact, flush eyes with water.

• Stop use and ask a doctor if redness or irritation develop and persist for more than 72 hours.

• Keep out of reach of children.

• Children should be supervised when using this product.

DIRECTIONS FOR USE:

Wipe liberally over the hands & body, rub into skin until dry. Recommended for single use.

INACTIVE INGREDIENTS:

Aloe Barbadensis leaf extract, Aqua, Citric Acid, Caprylyl Glucoside, Laureth 4, Polyhexanide, Phenoxyethanol, Triethoxysilylpropyl Steardimonium Chloride.

Questions?

Call +1(888) 331-8332, Mon-Fri 9:00AM-5:00PM (EST)

KILLS 99.99% OF HARMFUL GERMS

WITH SOOTHING ALOE VERA

LONG-LASTING, ALCOHOL-FREE PROTECTION FROM GERMS

Formulated and enhanced with Zetrisil™

A PROPRIETARY SILICONE QUATERNARY SOLUTION

FAST ACTING 15 SECOND FORMULA

BLEACH FREE

CAUTION

SEE BACK PANEL FOR PRECAUTIONARY STATEMENTS AND FIRST AID

100% LINT FREE

Please dispose of used wipes responsibly.

Do not dispose used wipes down the toilet.

DISTRIBUTED BY: ESC BRANDS, LLC.

664 OLD HARGRAVES ROAD, SUITE B

LEXINGTON NC 27295

888 331-8332

WWW.MY-SHIELD.COM

FORMULATED IN THE USA

MADE IN CHINA